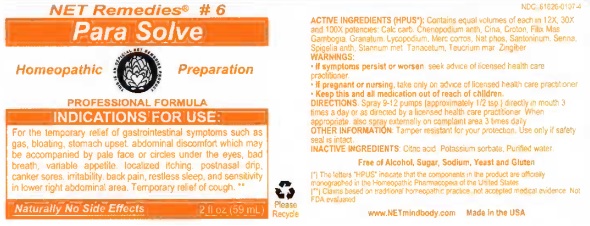 DRUG LABEL: Para Solve
NDC: 61626-0107 | Form: LIQUID
Manufacturer: NET Remedies
Category: homeopathic | Type: HUMAN PRESCRIPTION DRUG LABEL
Date: 20210119

ACTIVE INGREDIENTS: OYSTER SHELL CALCIUM CARBONATE, CRUDE 12 [hp_X]/59.1 mL; DYSPHANIA AMBROSIOIDES 12 [hp_X]/59.1 mL; ARTEMISIA CINA PRE-FLOWERING TOP 12 [hp_X]/59.1 mL; CROTON TIGLIUM SEED 12 [hp_X]/59.1 mL; DRYOPTERIS FILIX-MAS ROOT 12 [hp_X]/59.1 mL; GAMBOGE 12 [hp_X]/59.1 mL; PUNICA GRANATUM ROOT BARK 12 [hp_X]/59.1 mL; LYCOPODIUM CLAVATUM SPORE 12 [hp_X]/59.1 mL; MERCURIC CHLORIDE 12 [hp_X]/59.1 mL; SODIUM PHOSPHATE, DIBASIC, HEPTAHYDRATE 12 [hp_X]/59.1 mL; SANTONIN 12 [hp_X]/59.1 mL; SENNA LEAF 12 [hp_X]/59.1 mL; SPIGELIA ANTHELMIA 12 [hp_X]/59.1 mL; TIN 12 [hp_X]/59.1 mL; TANACETUM VULGARE TOP 12 [hp_X]/59.1 mL; TEUCRIUM MARUM 12 [hp_X]/59.1 mL; GINGER 12 [hp_X]/59.1 mL
INACTIVE INGREDIENTS: CITRIC ACID MONOHYDRATE; POTASSIUM SORBATE; WATER

Para Solve

ACTIVE INGREDIENT

ACTIVE INGREDIENTS (HPUS*): Contains equal volumes of each in 12X, 30X, and 100X potencies: Calc carb, Chenopodium anth, Cina, Croton, Filix Mas, Gambogia, Granatum, Lycopodium, Merc corros, Nat phos, Santoninum, Senna, Spigelia anth, Stannum met, Tanacetum, Teucrium mar, Zingiber.

(*) The letters "HPUS" indicate that the components in the product are officially monographed in the Homeopathic Pharmacopeia of the United States.

(**) Claims based on traditional homeopathic practice. Not accepted medical evidence. Not FDA evaluated.

INDICATIONS AND USAGE

INDICATIONS FOR USE: For the temporary relief of gastrointestinal symptoms such as gas, bloating, stomach upset, abdominal discomfort which may be accompanied by pale face or circles under the eyes, bad breath, bariable appetite, localized ithching, postnasal drip, canker sores. irritability, back pain, resltess sleep, and sensitivity in lower right abdominal area. Temporary relief of cough.**

WARNINGS:

• If symptoms persist or worsen, seek advice of licensed health care practicioner.

• If pregnant or nursing, take on only advice of licensed health care practicioner.

• Keep this and all medication out of reach of children.

KEEP OUT OF REACH OF CHILDREN

• Keep this and all medication out of reach of children.

DOSAGE AND ADMINISTRATION

DIRECTIONS: Spray 9-12 pumps (approximately 1/2 tsp.) directly in mouth 3 times a day or as directed by a licensed health care practicioner. When appropriate, also spray externally on complaint area 3 times daily.

OTHER INFORMATION: Tamper resistant for your protection. Use only if safetly seal is intact.

INACTIVE INGREDIENTS: Citric acid, Potassium sorbate, Purified water.

Free of Alcohol, Sugar, Sodium, Yeast and Gluten.

QUESTIONS

www.NETmindbody.com

Made in the USA.

PACKAGE LABEL

NET Remedies #6

Para Solve

Homeopathic Preparation

PROFESSIONAL FORMULA

Naturally No Side Effects

PURPOSE

INDICATIONS FOR USE: For the temporary relief of gastrointestinal symptoms such as gas, bloating, stomach upset, abdominal discomfort which may be accompanied by pale face or circles under the eyes, bad breath, bariable appetite, localized ithching, postnasal drip, canker sores. irritability, back pain, resltess sleep, and sensitivity in lower right abdominal area. Temporary relief of cough.**